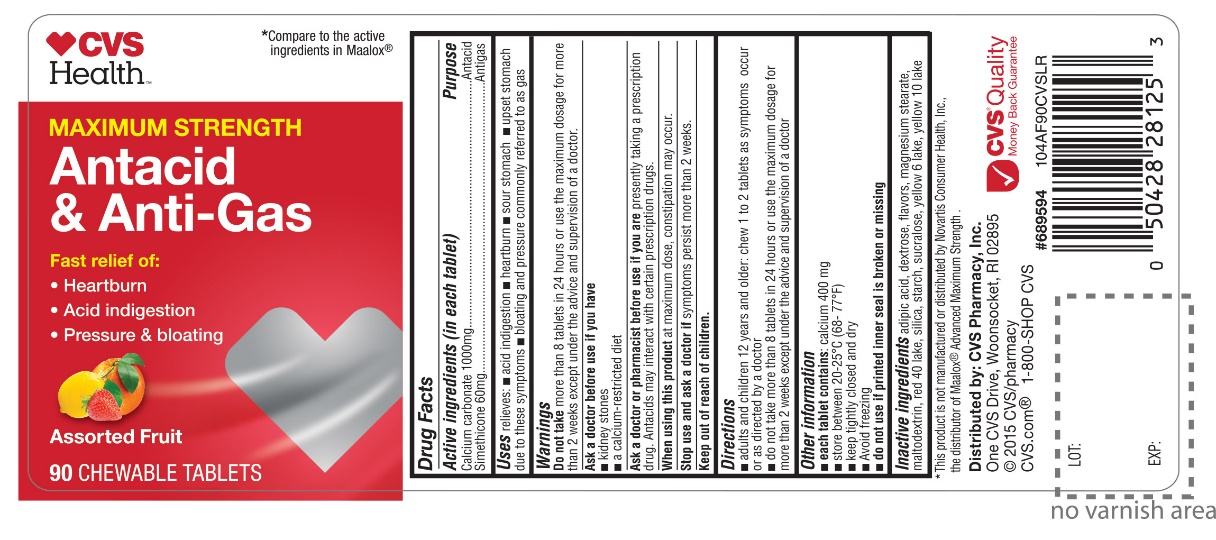 DRUG LABEL: CVS Health Maximum Strength
NDC: 59779-636 | Form: TABLET, CHEWABLE
Manufacturer: CVS Pharmacy,Inc.
Category: otc | Type: HUMAN OTC DRUG LABEL
Date: 20251204

ACTIVE INGREDIENTS: CALCIUM CARBONATE 1000 mg/1 1; DIMETHICONE, UNSPECIFIED 60 mg/1 1
INACTIVE INGREDIENTS: ADIPIC ACID; DEXTROSE, UNSPECIFIED FORM; MAGNESIUM STEARATE; MALTODEXTRIN; FD&C RED NO. 40; STARCH, CORN; SUCRALOSE; FD&C YELLOW NO. 6; D&C YELLOW NO. 10

CVS Health Maximum Strength Antacid and Anti-Gas

Active ingredients (in each tablet)

Calcium carbonate 1000 mg

Simethicone 60 mg

Purpose

Antacid

Antigas

Uses

relieves:

- acid indigestion
- heartburn
- sour stomach
- upset stomach due to these symptoms
- bloating and pressure commonly referred to as gas

Warnings

Do not takemore than 8 tablets in 24 hours or use the maximum dosage for more than 2 weeks except under the advice and supervision of a doctor.

Ask a doctor before use if you have

- kidney stones
- a calcium-restricted diet

Ask a doctor or pharmacist before use if you are

presently taking a prescription drug. Antacids may interact with certain prescription drugs.

When using this product

at maximum dose, constipation may occur.

Stop use and ask a doctor if

symptoms persist for more than 2 weeks.

Directions

- adults and children 12 years and older: chew 1 to 2 tablets as symptoms occur or as directed by a doctor
- do not take more than 8 tablets in 24 hours or use the maximum dosage for more than 2 weeks except under the advice and supervision of a doctor

Other information

- e ach tablet contains:calcium 400 mg
- store between 20-25°C (68-77°F)
- Keep tightly closed and dry
- Avoid freezing
- do not use if printed inner seal is broken or missing

Inactive ingredients

adipic acid, dextrose, flavors, magnesium stearate, maltodextrin, red 40 lake, ,starch, sucralose, yellow 6 lake, yellow 10 lake

Package/Label Principal Display Panel

CVS Health™

*Compare to the active ingredients in Maalox®.

NDC: 59779-636-90

MAXIMUM STRENGTH

Antacid & Anti-Gas

Fast relief of:

- Heartburn
- Acid indigestion
- Pressure & bloating
- Assorted Fruit

90 CHEWABLE TABLETS

Distributed by: CVS Pharmacy, Inc.

One CVS Drive,

Woonsocket, RI 02895

©2015 CVS/pharmacy

CVS.com®

1-800-SHOP CVS

CVS® Quality

Money Back Guarantee

*This product is not manufactured or distributed by Novartis Consumer Health, Inc., the distributor of Maalox® Advanced Maximum Strength.